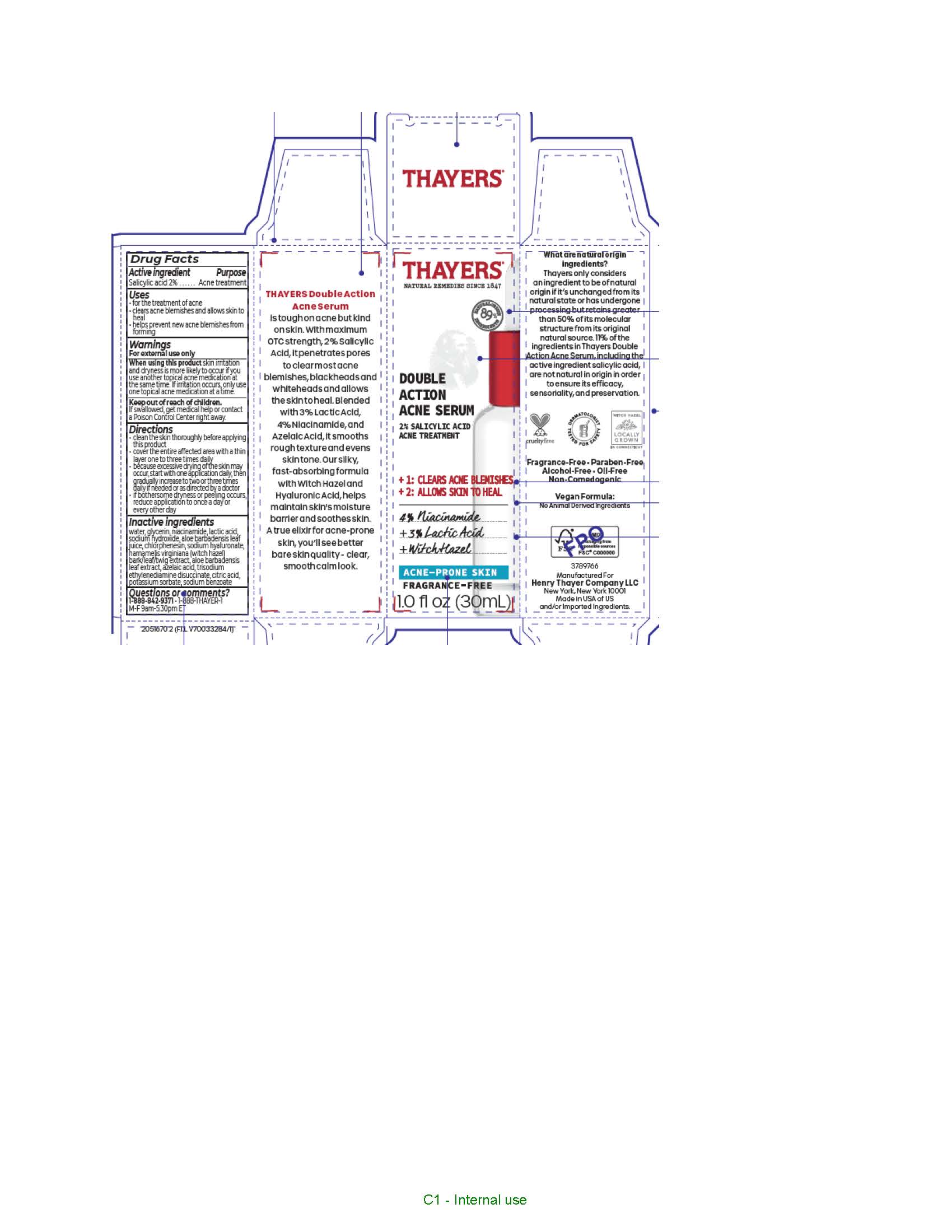 DRUG LABEL: Thayers Since 1847 Natural Remedies Double Action Acne Serum
NDC: 49967-062 | Form: SOLUTION
Manufacturer: L'Oreal USA Products Inc
Category: otc | Type: HUMAN OTC DRUG LABEL
Date: 20240717

ACTIVE INGREDIENTS: SALICYLIC ACID 20 mg/1 mL
INACTIVE INGREDIENTS: WATER; GLYCERIN; NIACINAMIDE; LACTIC ACID; SODIUM HYDROXIDE; ALOE VERA LEAF; CHLORPHENESIN; HYALURONATE SODIUM; HAMAMELIS VIRGINIANA TOP; AZELAIC ACID; TRISODIUM ETHYLENEDIAMINE DISUCCINATE; CITRIC ACID MONOHYDRATE; POTASSIUM SORBATE; SODIUM BENZOATE

Drug Facts

Active ingredient

Salicylic acid 2%

Purpose

Acne treatment

Uses

• for the treatment of acne
• clears acne blemishes and allows skin to heal
• helps prevent new acne blemishes from forming

Warnings

For external use only

When using this product

skin irritation and dryness is more likely to occur if you use another topical acne medication at the same time. If irritation occurs, only use one topical acne medication at a time.

Keep out of reach of children.

If swallowed, get medical help or contact a Poison Control Center right away.

Directions

- clean the skin thoroughly before applying this product
- cover the entire affected area with a thin layer one to three times daily
- because excessive drying of the skin may occur, start with one application daily, then gradually increase to two or three times daily if needed or as directed by a doctor
- if bothersome dryness or peeling occurs, reduce application to once a day or every other day

Inactive ingredients

water, glycerin, niacinamide, lactic acid, sodium hydroxide, aloe barbadensis leaf juice, chlorphenesin, sodium hyaluronate, hamamelis virginiana (witch hazel) bark/leaf/twig extract, aloe barbadensis leaf extract, azelaic acid, trisodium ethylenediamine disuccinate, citric acid, potassium sorbate, sodium benzoate

Questions or comments?

1-888-842-9371 1-888-THAYER-1

M-F 9am-5:30 pm ET